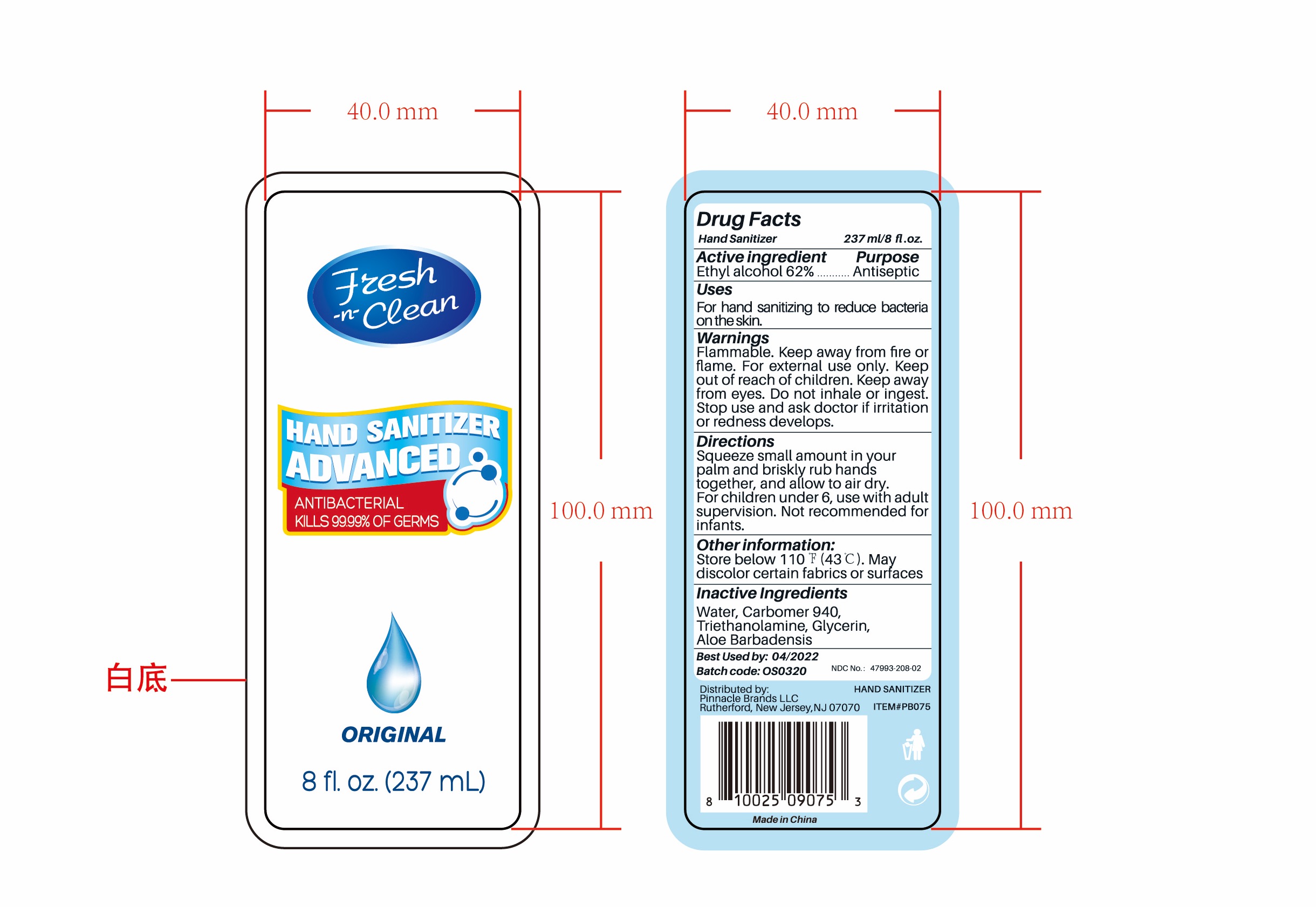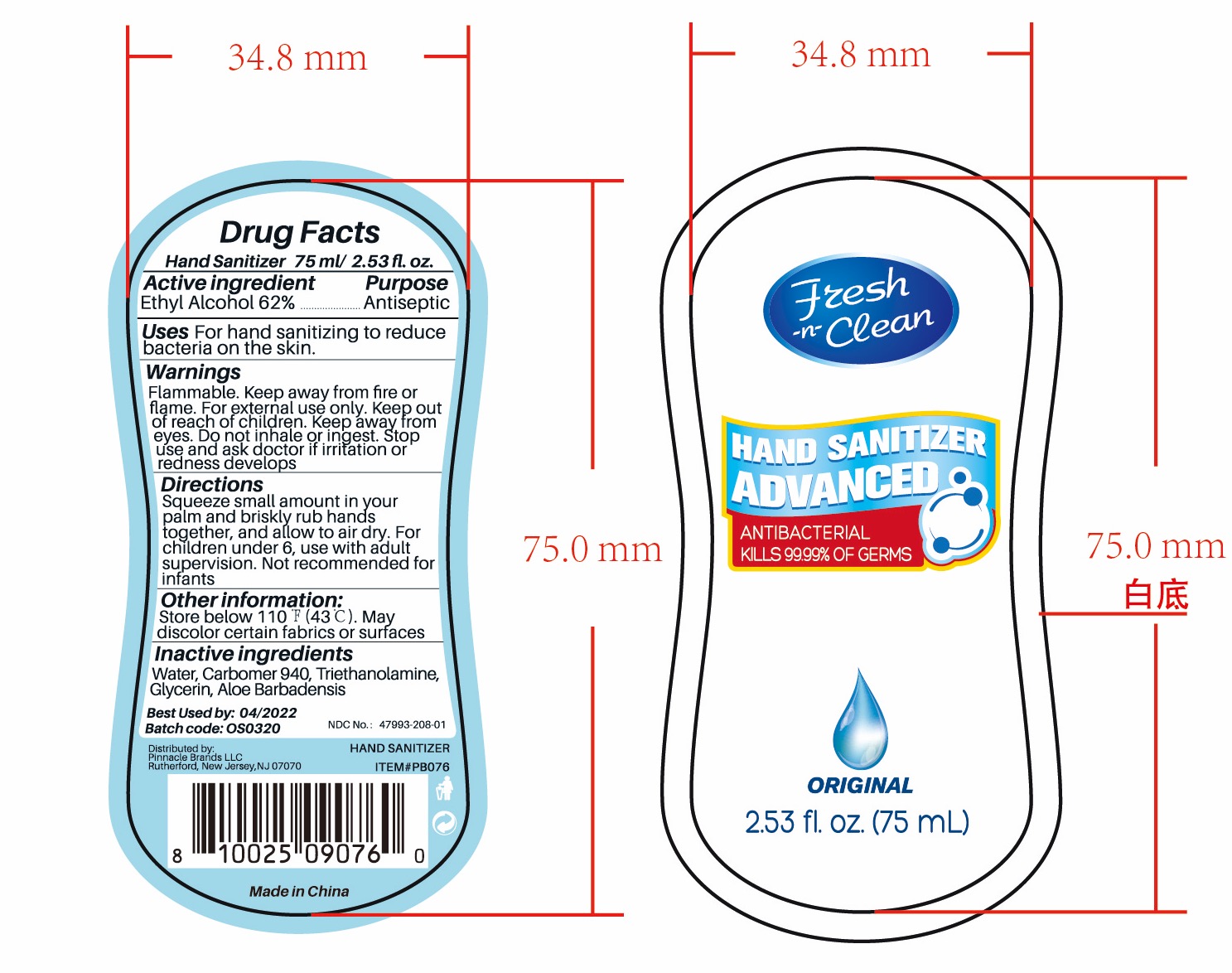 DRUG LABEL: HAND SANITIZER
NDC: 47993-209 | Form: GEL
Manufacturer: NINGBO JIANGBEI OCEAN STAR TRADING CO.,LTD
Category: otc | Type: HUMAN OTC DRUG LABEL
Date: 20201022

ACTIVE INGREDIENTS: ALCOHOL 62 g/89 mL
INACTIVE INGREDIENTS: CARBOMER 940 12 g/89 mL; TRIETHANOLAMINE BENZOATE 3 g/89 mL; GLYCERIN 2 g/89 mL; ALOE VERA LEAF 1 g/89 mL; WATER 20 g/89 mL

47993-209

Active ingredients--------------Purpose

Ethyl Alcohol 62%------------Antiseptic

Uses:
For hand sanitizing to reduce bacteria on the skin.

Warnings:

Flammable. Keep away from fire or flame. For external use only. Keep out of reach of children. Keep away from eyes. Do not inhale or ingest. Stop use and ask doctor if irritation or redness develops.

Directions:

Squeeze small amount in your palm and briskly rub hands together until dry. For children under 6, use with adult supervision. Not recommended for infants.

Other Information

Store below 110F(43C). May discolor certain fabrics or surfaces.

Keep out of reach of children.

Inactive ingredients

Water，Carbomer 940，Triethanolamine，Glycerin，Aloe Barbadensis